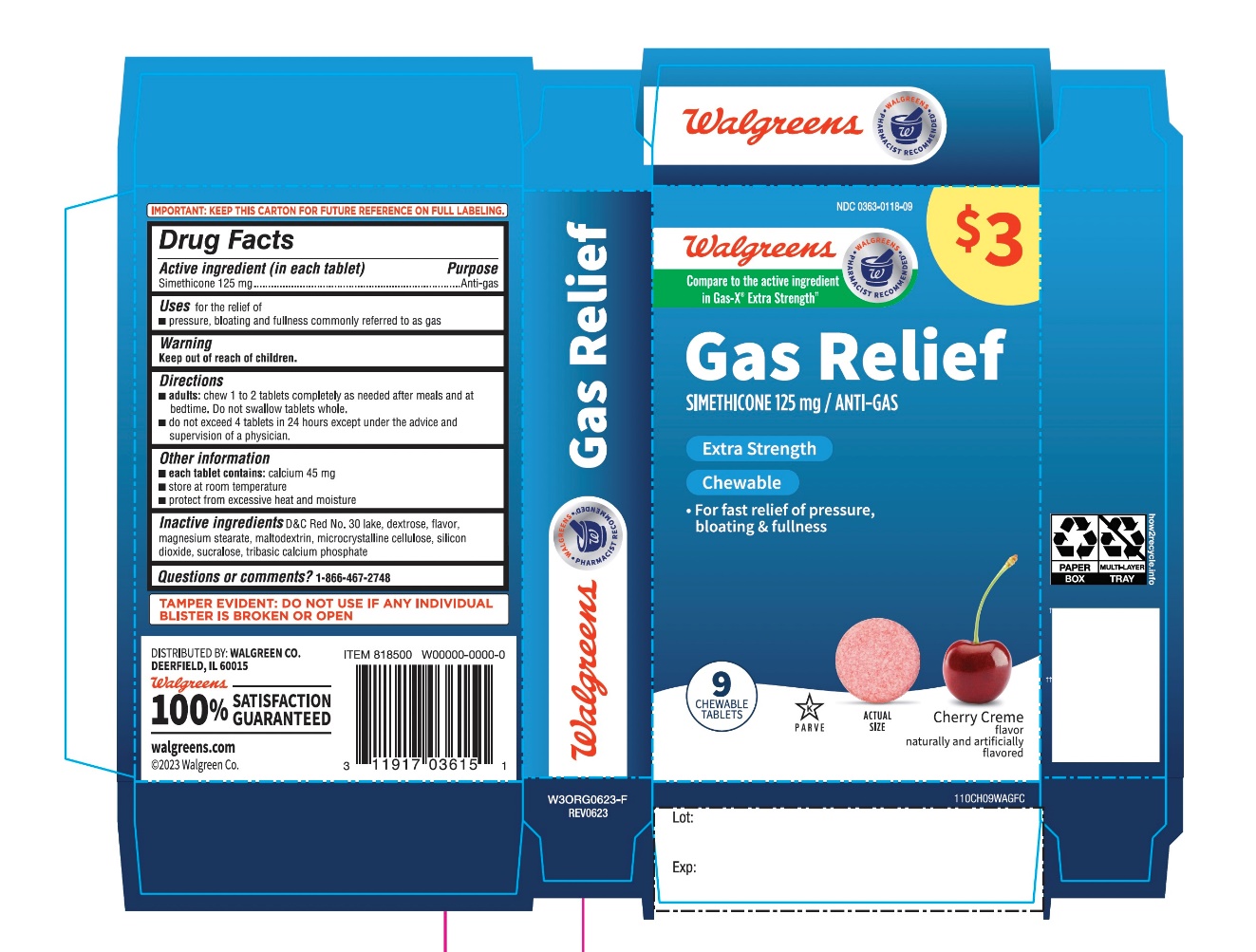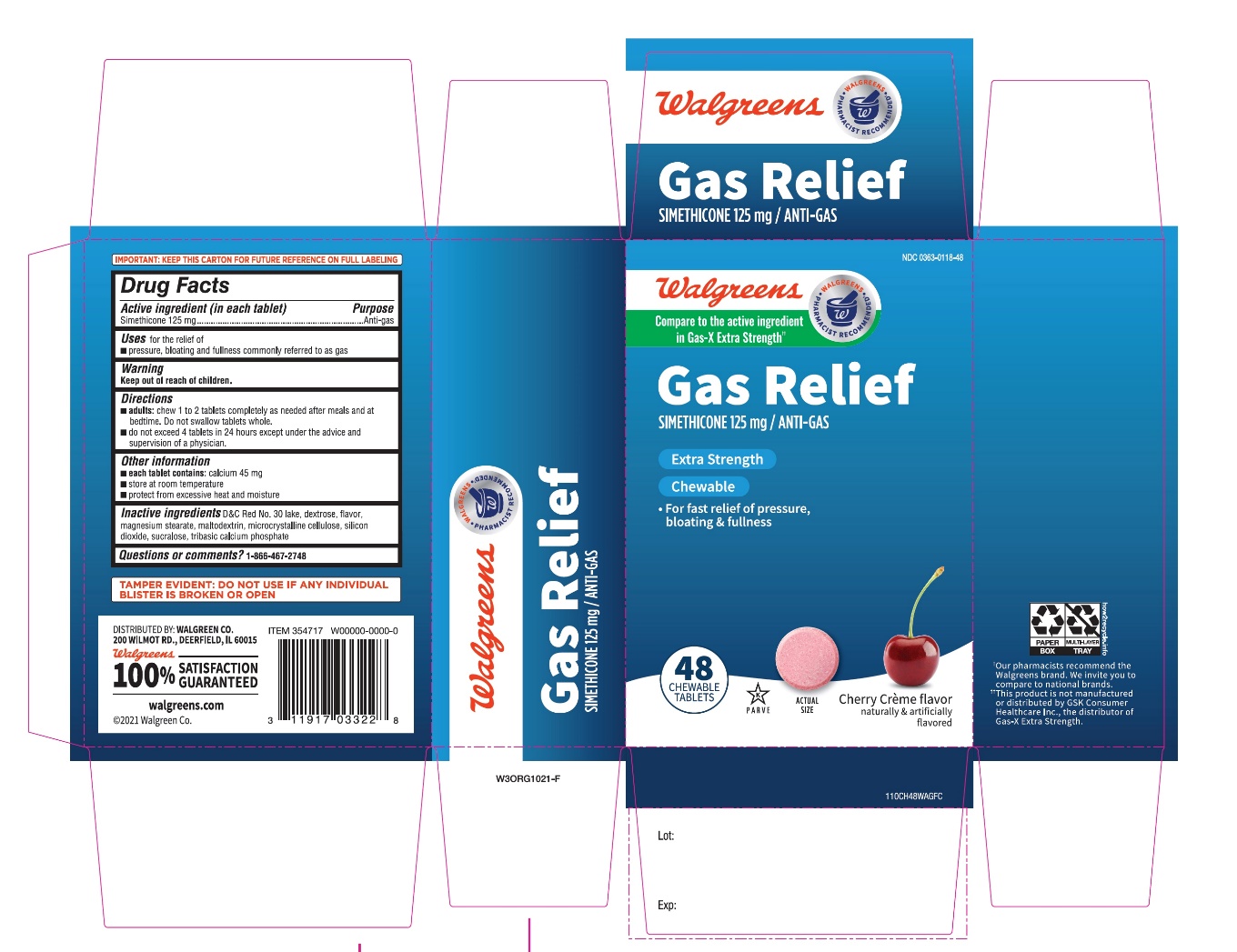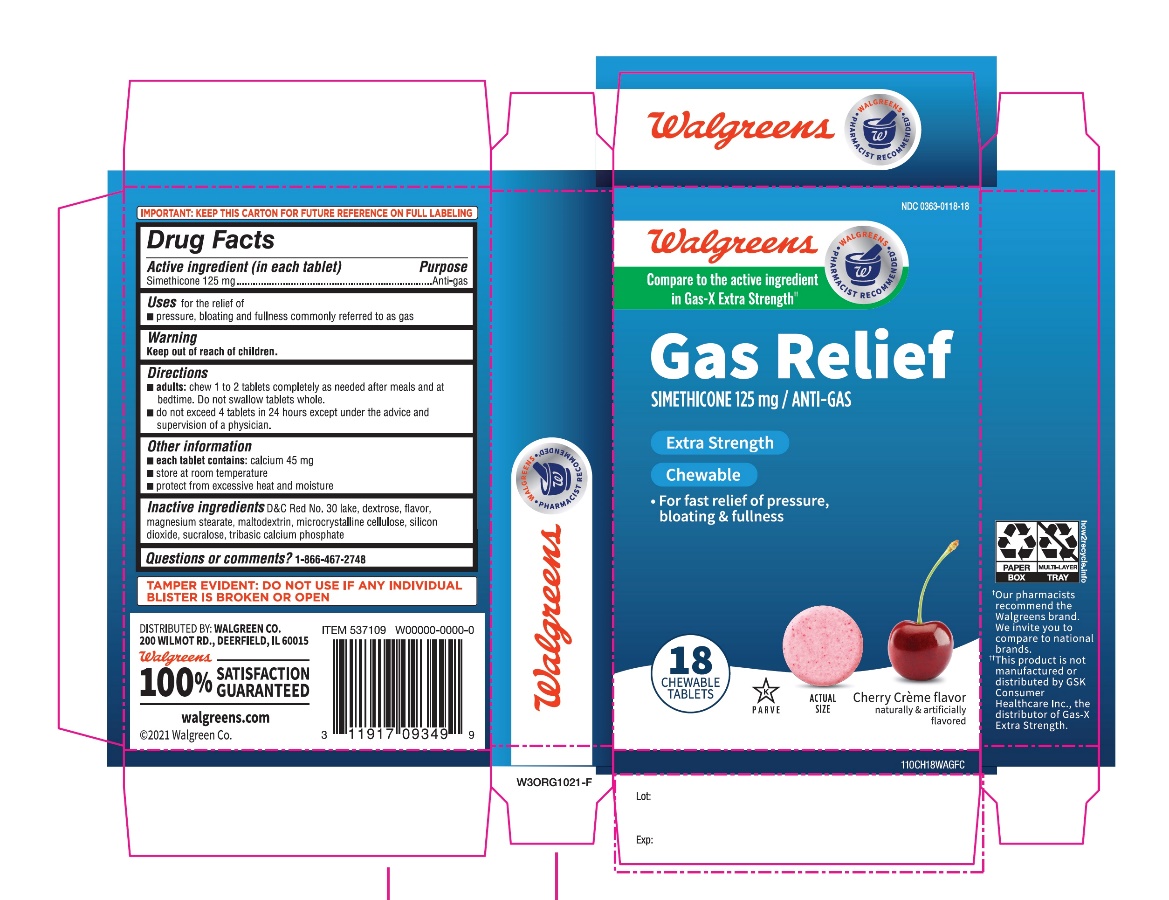 DRUG LABEL: Walgreens

NDC: 0363-0118 | Form: TABLET, CHEWABLE
Manufacturer: WALGREENS CO.
Category: otc | Type: HUMAN OTC DRUG LABEL
Date: 20251125

ACTIVE INGREDIENTS: DIMETHICONE, UNSPECIFIED 125 mg/1 1
INACTIVE INGREDIENTS: D&C RED NO. 30; DEXTROSE, UNSPECIFIED FORM; CHERRY; MAGNESIUM STEARATE; MALTODEXTRIN; MICROCRYSTALLINE CELLULOSE; SILICON DIOXIDE; SUCRALOSE; TRIBASIC CALCIUM PHOSPHATE; FD&C RED NO. 40

Walgreens Extra Strength Gas Relief Chewable Tablets

Active ingredient (in each tablet)

Simethicone 125 mg

Purpose

Anti-gas

Uses

for the relief of

- Pressure, bloating and fullness commonly referred to as gas

Directions

- adults: chew 1 to 2 tablets as needed after meals and at bedtime. Do not swallow tablets whole.
- do not exceed 4 tablets in a 24 hours except under the advice and supervision of a physician.

Other information

- each tablets contains:calcium 45 mg
- store at room temperature
- protect from excessive heat and moisture

DO NOT USE IF ANY INDVIDUAL BLISTER IS BROKEN OR OPEN

Inactive ingredients

D&C Red No. 30, dextrose, flavor, magnesium stearate, maltodextrin, microcrystalline cellulose, silicon dioxide, sucralose, tribasic calcium phosphate, FD&C red 40

Principal Display Panel

Walgreens

NDC 0363-0118-18

*Compare to GAS-X®Extra Strength active ingredient††

Gas Relief

SIMETHICONE 125 mg/ANTI-GAS

EXTRA STRENGTH

CHEWABLE

For fast relief of pressure, bloating & discomfort

CHERRY FLAVOR

NATURALLY AND ARTIFICIALLY FLAVORED

18 CHEWABLE TABLETS

K PAREVE

††This product is not manufactured or distributed by GSK Consumer Healthcare, Inc. the distributor of Gas-X®Extra strength.

DISTRIBUTED BY: WALGREEN CO.

200 WILMOT RD., DEERFIELD, IL 60015

Walgreens 100% SATISFACTION GUARANTEED

Walgreens.com ©2017 Walgreen Co.

MADE IN U.S.A.

IMPORTANT:Keep this carton for future reference on full labeling.